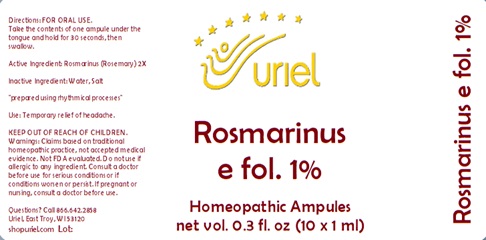 DRUG LABEL: Rosmarinus e fol. 1%
NDC: 48951-8409 | Form: LIQUID
Manufacturer: Uriel Pharmacy Inc.
Category: homeopathic | Type: HUMAN OTC DRUG LABEL
Date: 20240308

ACTIVE INGREDIENTS: ROSMARINUS OFFICINALIS FLOWERING TOP 2 [hp_X]/1 mL
INACTIVE INGREDIENTS: WATER; SODIUM CHLORIDE

Rosmarinus e fol. 1%

INDICATIONS AND USAGE

Directions: FOR ORAL USE.

DOSAGE AND ADMINISTRATION

Take the contents of one ampule under the tongue and hold for 30 seconds, then swallow.

Active Ingredient: Rosmarinus (Rosemary)2X

Inactive Ingredient: Water, Salt

"prepared using rhythmical processes"

PURPOSE

Use: Temporary relief of headache.

KEEP OUT OF REACH OF CHILDREN.

WARNINGS

Warnings: Claims based on traditional homeopathic practice, not accepted medical evidence. Not FDA evaluated. Do not use if allergic to any ingredient. Consult a doctor before use for serious conditions or if conditions worsen or persist. If pregnant or nursing, consult a doctor before use.

QUESTIONS

Questions? Call 866.642.2858 Uriel, East Troy, WI 53120 shopuriel.com Lot: